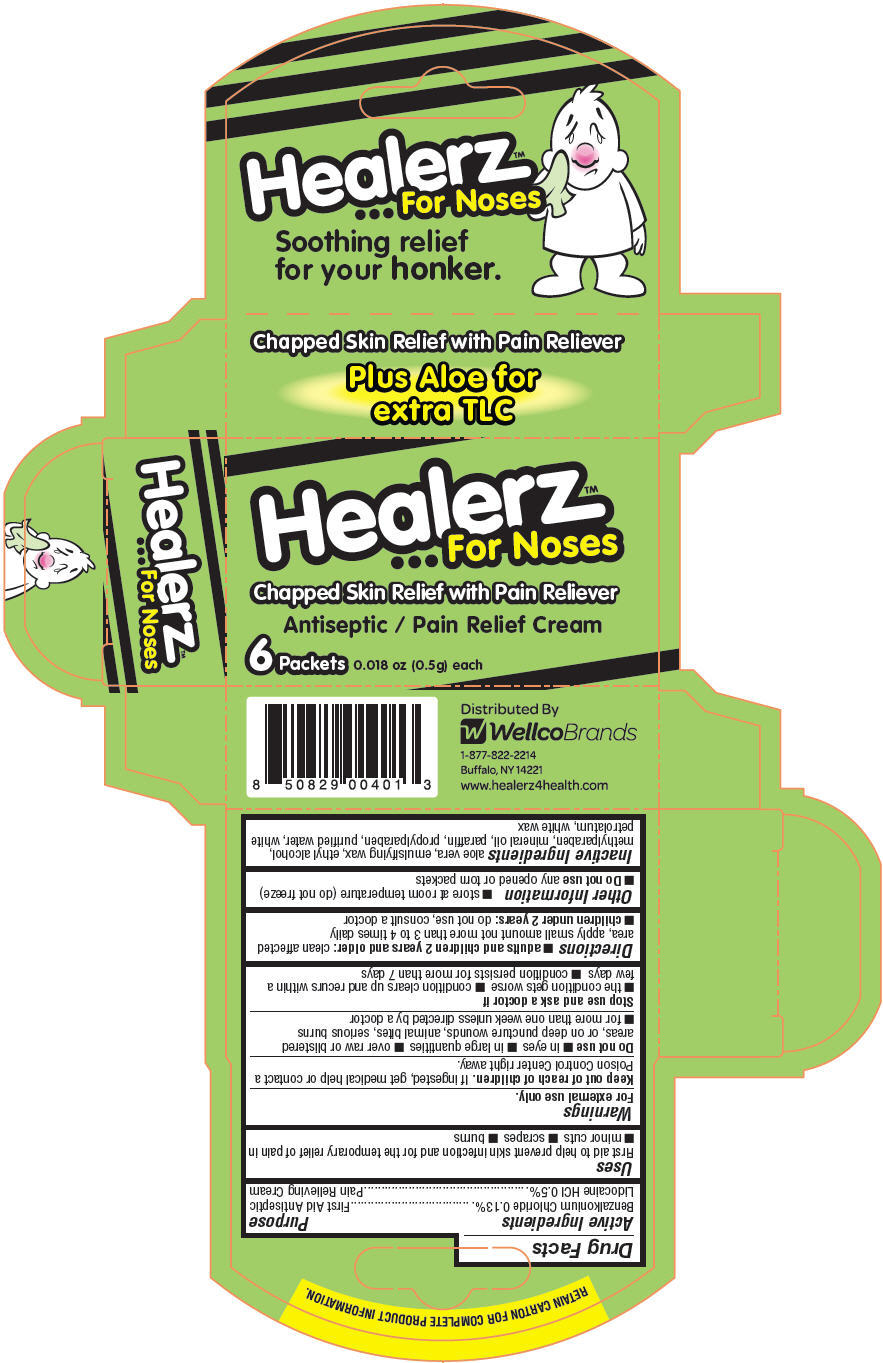 DRUG LABEL: Healerz for Noses
NDC: 50485-101 | Form: CREAM
Manufacturer: Wellco Brands LLC
Category: otc | Type: HUMAN OTC DRUG LABEL
Date: 20130510

ACTIVE INGREDIENTS: BENZALKONIUM CHLORIDE 1.3 mg/1 g; LIDOCAINE HYDROCHLORIDE 5 mg/1 g
INACTIVE INGREDIENTS: ALOE VERA LEAF; ALCOHOL; METHYLPARABEN; MINERAL OIL; PARAFFIN; PROPYLPARABEN; WATER; PETROLATUM; WHITE WAX

Healerz™... for Noses

Drug Facts

ACTIVE INGREDIENT

Active Ingredients | Purpose
Benzalkonium Chloride 0.13% | First Aid Antiseptic
Lidocaine HCl 0.5% | Pain Relieving Cream

Uses

First aid to help prevent skin infection and for the temporary relief of pain in

- minor cuts
- scrapes
- burns

Warnings

For external use only.

Keep out of reach of children. If ingested, get medical help or contact a Poison Control Center right away.

Do not use

- in eyes
- in large quantities
- over raw or blistered areas, or on deep puncture wounds, animal bites, serious burns
- for more than one week unless directed by a doctor

Stop use and ask a doctor if

- the condition gets worse
- condition clears up and recurs within a few days
- condition persists for more than 7 days

Directions

- adults and children 2 years and older: clean affected area, apply small amount not more than 3 to 4 times daily
- children under 2 years: do not use, consult a doctor

Other Information

- store at room temperature (do not freeze)
- Do not use any opened or torn packets

Inactive Ingredients

aloe vera, emulsifying wax, ethyl alcohol, methylparaben, mineral oil, paraffin, propylparaben, purified water, white petrolatum, white wax

Distributed By
Wellco Brands
Buffalo, NY 14221

PRINCIPAL DISPLAY PANEL - 0.5 g Packet Box

Healerz™
... For Noses

Chapped Skin Relief with Pain Reliever

Antiseptic / Pain Relief Cream

6Packets 0.018 oz (0.5g) each